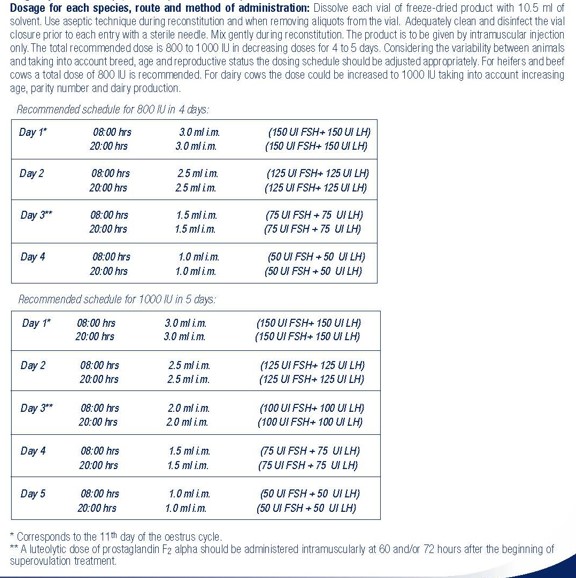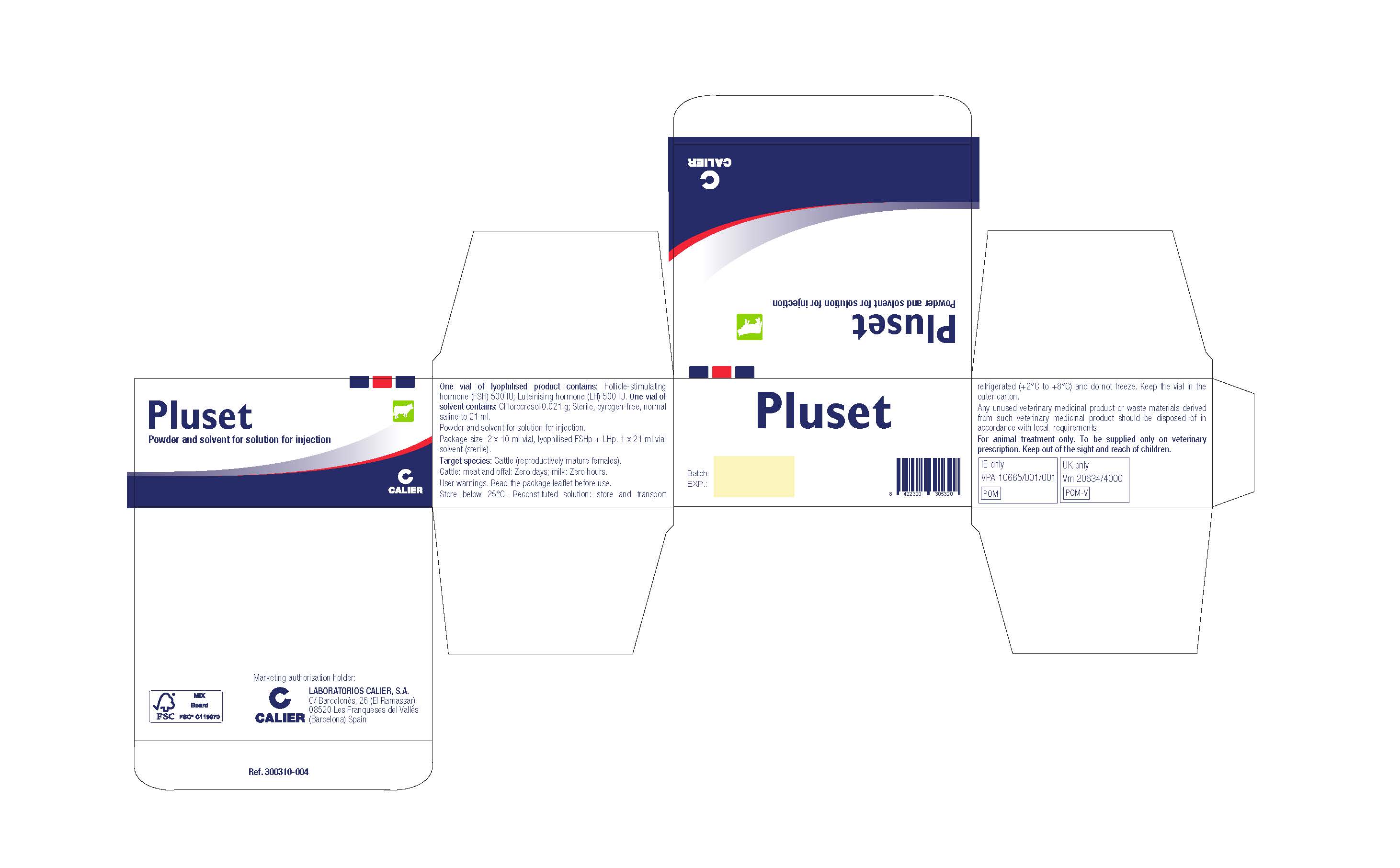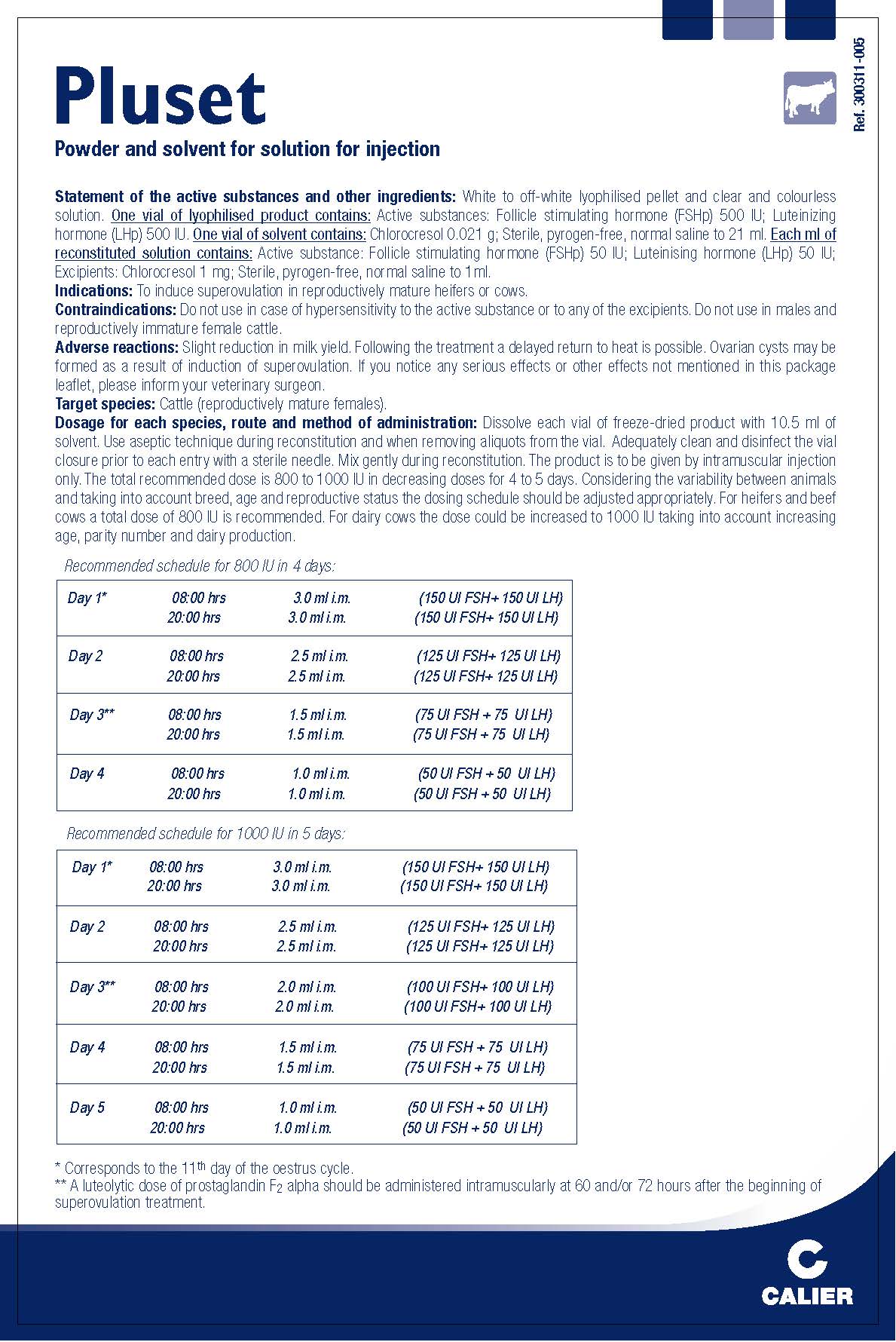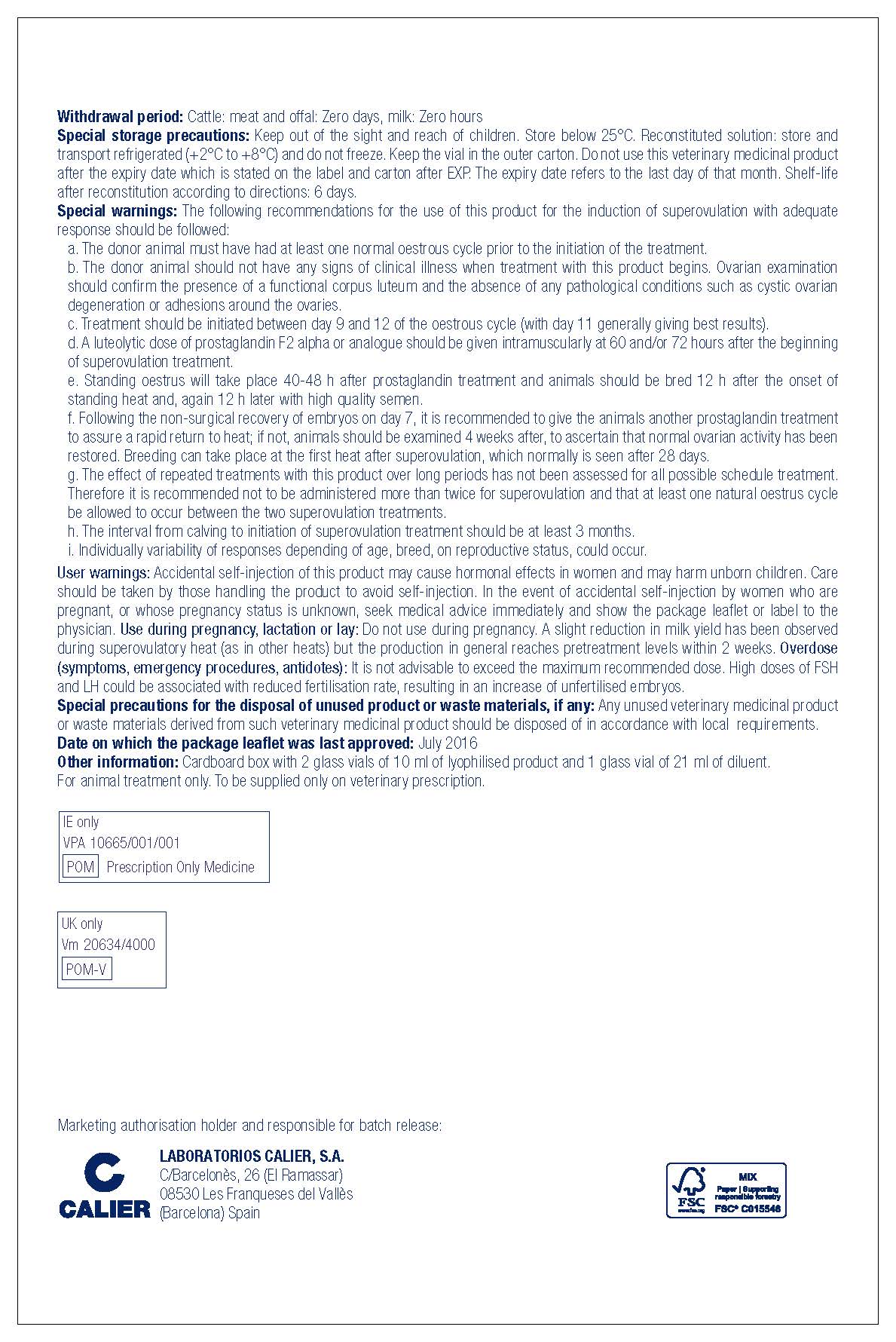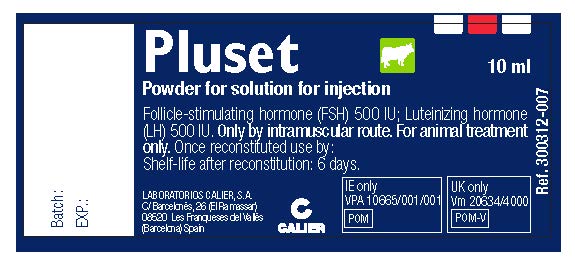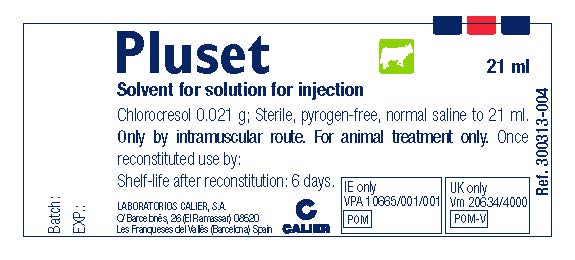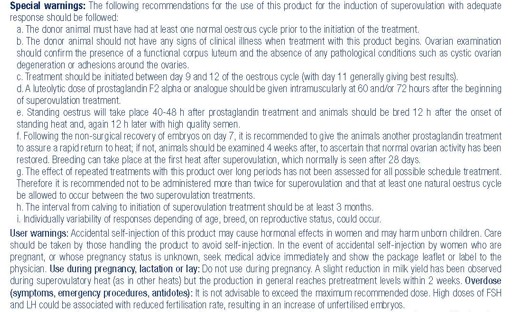 DRUG LABEL: PLUSET
NDC: 76307-101 | Form: KIT | Route: INTRAMUSCULAR
Manufacturer: Laboratorios Calier S.A.
Category: animal | Type: PRESCRIPTION ANIMAL DRUG LABEL
Date: 20240108

ACTIVE INGREDIENTS: FOLLICLE STIMULATING HORMONE (PORCINE) 50 [iU]/1 mL; LUTEINIZING HORMONE 50 [iU]/1 mL
INACTIVE INGREDIENTS: CHLOROCRESOL 0.021 g/1 mL; SODIUM CHLORIDE; WATER

PLUSET

Indications:

To induce superovulation in reproductively mature heifers or cows.

Contraindications:

Do not use in case of hypersensitivity to the active substance or to any of the excipients. Do not use in males and reproductively immature female cattle.

Adverse reactions:

Slight reduction in milk yield. Following the treatment a delayed return to heat is possible. Ovarian cysts may be formed as a result of induction of superovulation. If you notice any serious effects or other effects not mentioned in this package leaflet, please inform your veterinary surgeon.

Withdrawal period:

Cattle: meat and offal: zero days; milk: zero hours

Special storage precautions:

Keep out of the sight and reach of children. Store below 25°C. Reconstituted solution: store and transport refrigerated (+2°C to +8°C) and do not freeze. Keep the vial in the outer carton. Do not use this veterinary medicinal product after the expiry date which is stated on the label and carton after EXP. The expiry date refers to the last day of that month. Shelf-life after reconstitution according to directions: 6 days.

Special precautions for the disposal of unused product or waste materials, if any:

Any unused veterinary medicinal product or waste materials derived from such veterinary medicinal product should be disposed of in accordance with local requirements.

Other information:

Carboard box with 2 glass vials of 10ml of lyophilised product and 1 glass vial of 21ml of diluent.

For animal treatment only. To be supplied only on veterinary prescription.